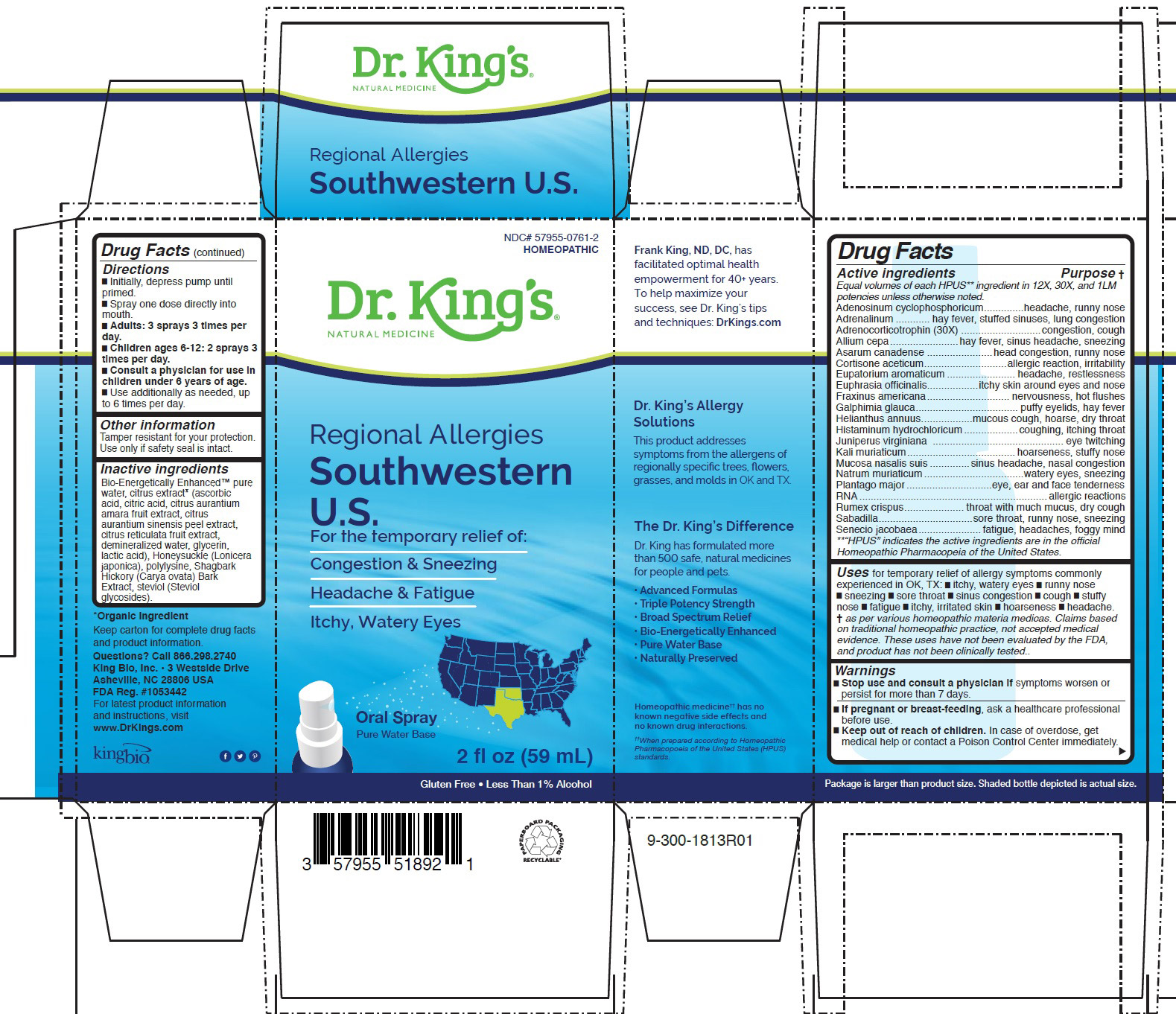 DRUG LABEL: Regional Allergies Southwestern U.S.
NDC: 57955-0761 | Form: LIQUID
Manufacturer: King Bio Inc.
Category: homeopathic | Type: HUMAN OTC DRUG LABEL
Date: 20200709

ACTIVE INGREDIENTS: ADENOSINE CYCLIC PHOSPHATE 12 [hp_X]/59 mL; EPINEPHRINE 12 [hp_X]/59 mL; CORTICOTROPIN 30 [hp_X]/59 mL; ONION 12 [hp_X]/59 mL; ASARUM CANADENSE ROOT 12 [hp_X]/59 mL; CORTISONE ACETATE 12 [hp_X]/59 mL; AGERATINA AROMATICA ROOT 12 [hp_X]/59 mL; EUPHRASIA STRICTA 12 [hp_X]/59 mL; FRAXINUS AMERICANA BARK 12 [hp_X]/59 mL; GALPHIMIA GLAUCA FLOWERING TOP 12 [hp_X]/59 mL; HELIANTHUS ANNUUS FLOWERING TOP 12 [hp_X]/59 mL; HISTAMINE DIHYDROCHLORIDE 12 [hp_X]/59 mL; JUNIPERUS VIRGINIANA TWIG 12 [hp_X]/59 mL; POTASSIUM CHLORIDE 12 [hp_X]/59 mL; SUS SCROFA NASAL MUCOSA 12 [hp_X]/59 mL; SODIUM CHLORIDE 12 [hp_X]/59 mL; PLANTAGO MAJOR 12 [hp_X]/59 mL; SACCHAROMYCES CEREVISIAE RNA 12 [hp_X]/59 mL; RUMEX CRISPUS ROOT 12 [hp_X]/59 mL; SCHOENOCAULON OFFICINALE SEED 12 [hp_X]/59 mL; JACOBAEA VULGARIS 12 [hp_X]/59 mL
INACTIVE INGREDIENTS: WATER; CARYA OVATA BARK; CITRUS BIOFLAVONOIDS; LONICERA JAPONICA FLOWER; POLYEPSILON-LYSINE (4000 MW); REBAUDIOSIDE A

Regional Allergies Southwestern U.S.

ACTIVE INGREDIENT

Drug Facts__________________________________________________________________________________________________________

HPUS active ingredients: Adenosinum cyclophosphoricum, Adrenalinum, Adrenocorticotrophin (30X), Allium cepa, Asarum canadense, Cortisone aceticum, Eupatorium aromaticum, Euphrasia officinalis, Fraxinus americana, Galphimia glauca, Helianthus annuus, Histaminum hydrochloricum, Juniperus virginiana, Kali muriaticum, Mucosa nasalis suis, Natrum muriaticum, Plantago major, RNA, Rumex crispus, Sabadilla, Senecio jacobaea. Equal volumes of each ingredient in 12X, 30X, and 1LM potencies.

INDICATIONS AND USAGE

Uses for temporary relief of allergy symptoms commonly
experienced in OK, TX: █ itchy, watery eyes █ runny nose
█ sneezing █ sore throat █ sinus congestion █ cough █ stuffy
nose █ fatigue █ itchy, irritated skin █ hoarseness █ headache.
† as per various homeopathic materia medicas. Claims based
on traditional homeopathic practice, not accepted medical
evidence. These uses have not been evaluated by the FDA,
and product has not been clinically tested..

WARNINGS

WarningsStop use and consult a physician if symptoms worsen or
persist for more than 7 days.

PREGNANCY OR BREAST FEEDING

If pregnant or breast-feeding, ask a healthcare professional
before use.

Keep out of reach of children. In case of overdose, get
medical help or contact a Poison Control Center immediately

Directions

█ Initially, depress pump until
primed.
█ Spray one dose directly into
mouth.
█ Adults: 3 sprays 3 times per
day.
█ Children ages 6-12: 2 sprays 3
times per day.
█ Consult a physician for use in
children under 6 years of age.
█ Use additionally as needed, up
to 6 times per day

Other information: Tamper resistant for your protection. Use only if safety seal is intact.

Inactive Ingredients:

Bio-Energetically Enhanced™ pure
water, citrus extract* (ascorbic
acid, citric acid, citrus aurantium
amara fruit extract, citrus
aurantium sinensis peel extract,
citrus reticulata fruit extract,
demineralized water, glycerin,
lactic acid), Honeysuckle (Lonicera
japonica), polylysine, Shagbark
Hickory (Carya ovata) Bark
Extract, steviol (Steviol
glycosides).

Drug Facts

____________________________________________________________________________________________________________

HPUS active ingredients Purpose

Equal volumes of each HPUS** ingredient in 12X, 30X, and 1LM
potencies unless otherwise noted.
Adenosinum cyclophosphoricum..............headache, runny nose
Adrenalinum ............ hay fever, stuffed sinuses, lung congestion
Adrenocorticotrophin (30X) ............................congestion, cough
Allium cepa........................hay fever, sinus headache, sneezing
Asarum canadense .......................head congestion, runny nose
Cortisone aceticum.............................allergic reaction, irritability
Eupatorium aromaticum ........................ headache, restlessness
Euphrasia officinalis..................itchy skin around eyes and nose
Fraxinus americana............................. nervousness, hot flushes
Galphimia glauca.................................... puffy eyelids, hay fever
Helianthus annuus..................mucous cough, hoarse, dry throat
Histaminum hydrochloricum...................coughing, itching throat
Juniperus virginiana .............................................. eye twitching
Kali muriaticum......................................hoarseness, stuffy nose
Mucosa nasalis suis ..............sinus headache, nasal congestion
Natrum muriaticum...................................watery eyes, sneezing
Plantago major..............................eye, ear and face tenderness
RNA..................................................................allergic reactions
Rumex crispus..................... throat with much mucus, dry cough
Sabadilla.................................sore throat, runny nose, sneezing
Senecio jacobaea......................fatigue, headaches, foggy mind
**“HPUS” indicates the active ingredients are in the official
Homeopathic Pharmacopeia of the United States.

Questions? Call 866.298.2740
King Bio, Inc. • 3 Westside Drive
Asheville, NC 28806 USA
FDA Reg. #1053442

For latest product information
and instructions, visit
www.DrKings.com